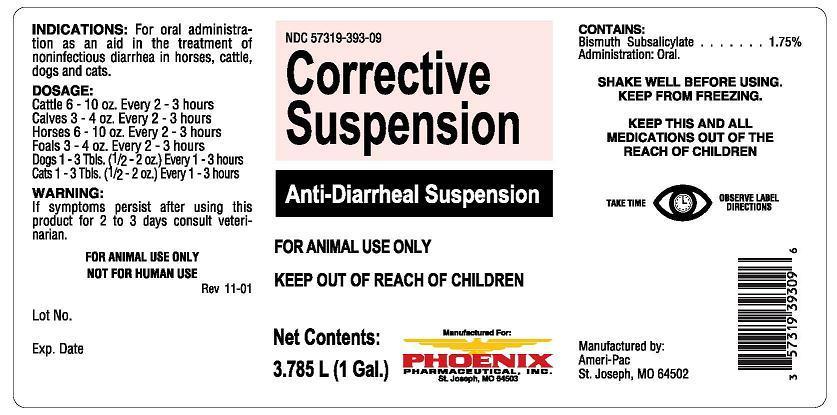 DRUG LABEL: Corrective
NDC: 57319-393 | Form: SUSPENSION
Manufacturer: Phoenix Pharmaceutical Inc./ Clipper Distributing, Inc.
Category: animal | Type: OTC ANIMAL DRUG LABEL
Date: 20130917

ACTIVE INGREDIENTS: BISMUTH SUBSALICYLATE 18 mg/1 mL
INACTIVE INGREDIENTS: WATER; GUAR GUM; METHYL SALICYLATE; POTASSIUM SORBATE; SACCHARIN SODIUM; D&C RED NO. 33; SILICON DIOXIDE

Corrective Suspension
Anti-Diarrheal Suspension

NDC 57319-393-09 Corrective Suspension Anti-Diarrheal Suspension

FOR ANIMAL USE ONLY

KEEP OUT OF REACH OF CHILDREN

Net Contents:

3.785L (1 Gal.)

Manufactured For:

PHOENIX

PHARMACEUTICAL, INC.

St. Joseph, MO 64503

INDICATIONS:

For oral administration as an aid in the treatment of noninfectious diarrhea in horses, cattle, dogs and cats.

DOSAGE:

Cattle 6 - 10 oz. Every 2 - 3 hours
Calves 3 - 4 oz. Every 2 - 3 hours
Horses 6 - 10 oz. Every 2 - 3 hours
Foals 3 - 4 oz. Every 2 - 3 hours
Dogs 1 - 3 Tbls. (1/2 - 2 oz.) Every 1 - 3 hours
Cats 1 - 3 Tbls. (1/2 - 2 oz.) Every 1 - 3 hours

WARNING:

If symptoms persist after using this product for 2 to 3 days consult a veterinarian.

FOR ANIMAL USE ONLY

NOT FOR HUMAN USE

Rev 11-01

Lot No.

Exp. Date

CONTAINS:

Bismuth Subsalicylate ........... 1.75%

Administration: Oral.

KEEP THIS AND ALL MEDICATIONS OUT OF THE REACH OF CHILDREN

TAKE TIME OBSERVE LABEL DIRECTIONS

Manufactured by:
Ameri-Pac
St. Joseph, MO 64502